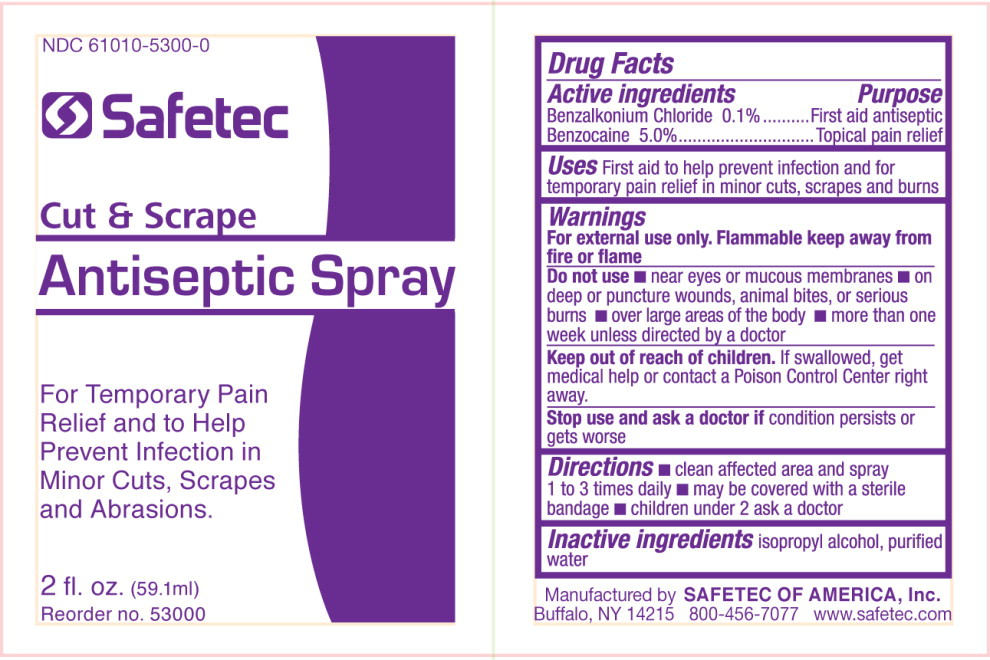 DRUG LABEL: Antiseptic
NDC: 84269-3501 | Form: SPRAY
Manufacturer: Wildman Business Group
Category: otc | Type: HUMAN OTC DRUG LABEL
Date: 20240901

ACTIVE INGREDIENTS: BENZOCAINE 50 mg/1 g; BENZALKONIUM CHLORIDE 1 mg/1 g
INACTIVE INGREDIENTS: ISOPROPYL ALCOHOL; WATER

84269-3501, Cut and Scrape Antiseptic

Drug Facts

Active Ingredients

Benzalkonium Chloride 0.1%

Benzocaine 5.0%

Purpose

First Aid Antiseptic

Topical Pain Relief

Uses

First aid to help prevent infection and for temporary pain relief in minor cuts, scrapes and burns

Warnings

For external use only. Flammable keep away from fire or flame.

Do not use

- near eyes or mucous membranes
- on deep or puncture wounds, animal bites, or serious burns
- over large areas of the body
- more than one week unless directed by a doctor

Keep out of reach of children.If swallowed get medical help or contact a Poison Control Center right away.

Stop use and ask doctor ifcondition persists or gets worse

Directions

- clean affected and spray 1 to 3 times daily
- may be covered with a sterile bandage
- children under 2 ask a doctor.

Inactive ingredients

isopropyl alcohol, purified water

PRINCIPAL DISPLAY PANEL – bottle label

NDC 61010-5300-0

Safetec

Cut & Scrape
Antiseptic Spray

For Temporary Pain
Relief and to Help
Prevent Infection in
Minor Cuts, Scrapes
and Abrasions.

2 fl. oz. (59.1ml)
Reorder no. 53000